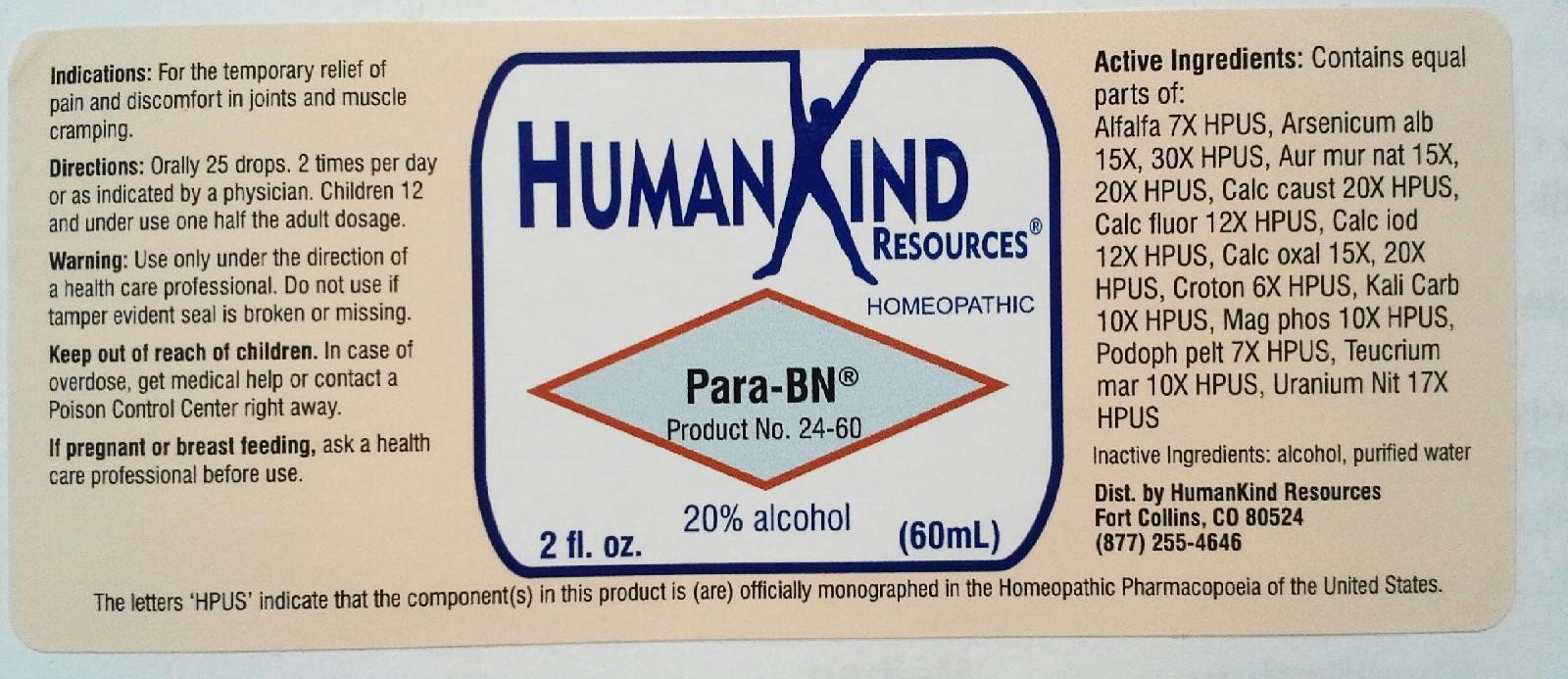 DRUG LABEL: Para-BN
NDC: 64616-102 | Form: LIQUID
Manufacturer: Vitality Works, Inc.
Category: homeopathic | Type: HUMAN OTC DRUG LABEL
Date: 20251217

ACTIVE INGREDIENTS: ALFALFA 7 [hp_X]/1 mL; ARSENIC TRIOXIDE 30 [hp_X]/1 mL; SODIUM TETRACHLOROAURATE 20 [hp_X]/1 mL; CALCIUM HYDROXIDE 20 [hp_X]/1 mL; CALCIUM FLUORIDE 12 [hp_X]/1 mL; CALCIUM IODIDE 12 [hp_X]/1 mL; CALCIUM OXALATE MONOHYDRATE 20 [hp_X]/1 mL; CROTON TIGLIUM SEED 6 [hp_X]/1 mL; POTASSIUM CARBONATE 10 [hp_X]/1 mL; MAGNESIUM PHOSPHATE, DIBASIC TRIHYDRATE 10 [hp_X]/1 mL; PODOPHYLLUM 7 [hp_X]/1 mL; TEUCRIUM MARUM 10 [hp_X]/1 mL; URANYL NITRATE HEXAHYDRATE 17 [hp_X]/1 mL
INACTIVE INGREDIENTS: WATER; ALCOHOL

Para-BN

Para-BN

Alfalfa 7X Croton Tiglium 6X

Arsenicum Album 15X, 30X Kali Carbonicum 10X

Aurum Muriaticum Natronatum 15X, 20X Magnesium Phosphoricum 10X

Calcarea Caustica 20X Podophyllum Peltatum 7X

Calcarea Fluorica 12X Teucrium Marum 10X

Calcarea Iodata 12X Uranium Nitricum 17X

Calcarea Oxalica 15X, 20X

Para-BN

Alcohol, Purified Water

Para-BN

Use only under the direction of a health care professional. Do not use if tamper evident seal is broken or missing.

Para-BN

Keep out of reach of children. In case of overdose, get medical help or contact a Poison Control Center right away.

Para-BN

For the temporary relief of pain and discomfort in joints and muscle cramping

Para-BN

Orally 25 drops, 2 times per day or as indicated by a physician. Children 12 and under use one falf the adult dosage.

Para-BN

For regulation of calcium absorption.